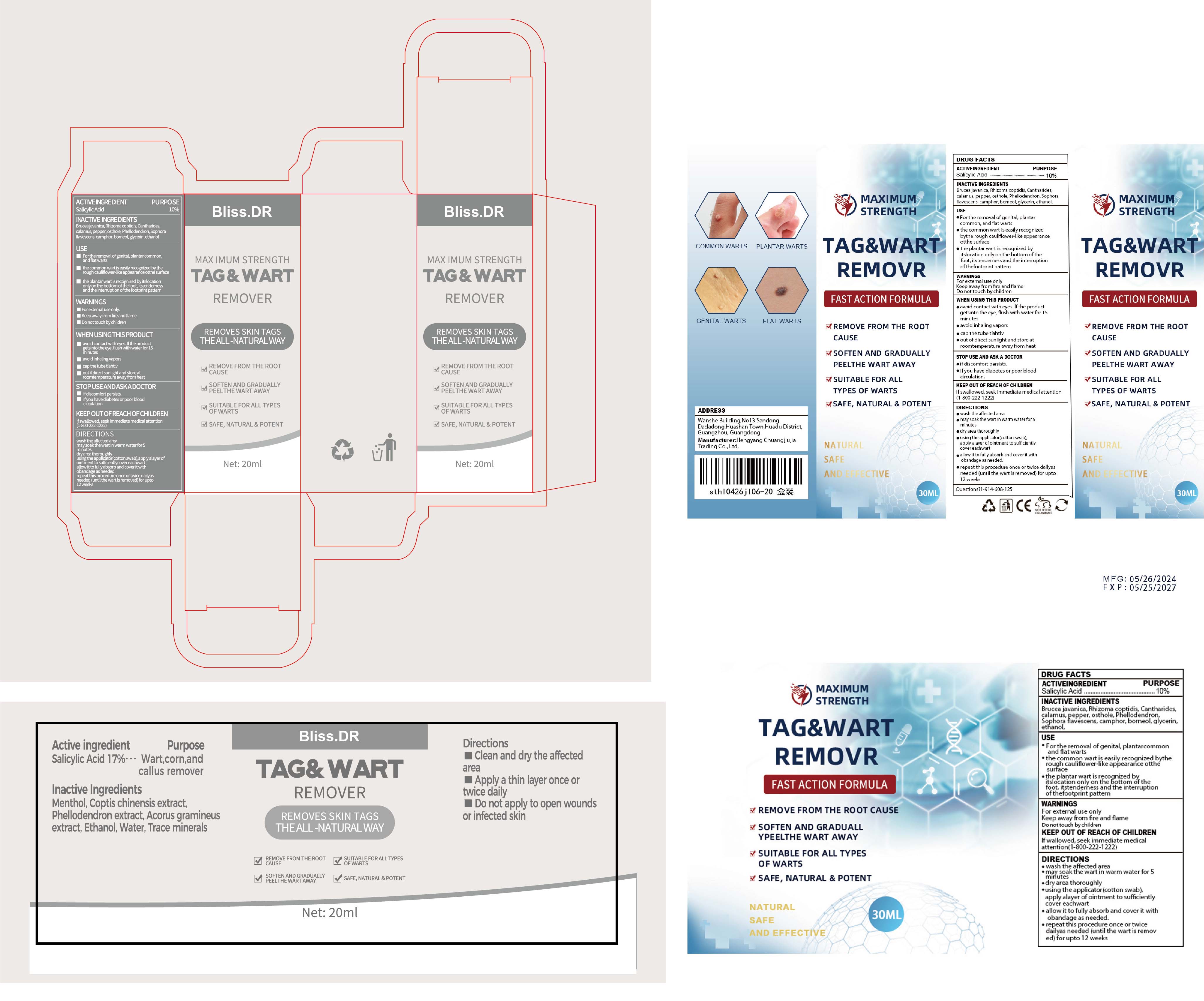 DRUG LABEL: Tag wart remover
NDC: 84735-004 | Form: LIQUID
Manufacturer: Hengyang Chuangjiujia Trading Co., Ltd.
Category: otc | Type: HUMAN OTC DRUG LABEL
Date: 20250806

ACTIVE INGREDIENTS: SALICYLIC ACID 10 g/100 mL
INACTIVE INGREDIENTS: LYTTA VESICATORIA; ACORUS CALAMUS ROOT; BORNEOL; GLYCERIN; BRUCEA JAVANICA WHOLE; COPTIS TEETA ROOT; PHELLODENDRON AMURENSE WHOLE; ALCOHOL; OSTHOL; SOPHORA FLAVESCENS ROOT; BLACK PEPPER; CAMPHOR (NATURAL)

84735-004 Tag & wart remover

ACTIVE INGREDIENT

salicylic acid 10%

PURPOSE

Removing warts

INDICATIONS AND USAGE

For the removal of genital, plantarcommon, and fat warts
the common wart is easily recognizedbythe rough cauliflower-like appearanceotthe surface
the plantar wart is recognized byitslocation only on the bottom of thefoot, itstenderness and the interruptionof thefootprint pattern

WARNINGS

For external use only
Keep away from fire and flame
Do not touch by children

WHEN USING

avoid contact with eyes. lf the productgetsinto the eye, flush with water for 15minutes
eavoid inhaling vapors
cap the tube tiahtlv
out of direct sunlight and store atroomtemperature away from heat

STOP USE

if discomfort persists.
if you have diabetes or poor bloodcirculation.

KEEP OUT OF REACH OF CHILDREN

If swallowed, seekimmediate medical attention (1-800-222-1222)

DOSAGE AND ADMINISTRATION

wash the affected area
may soak the wart in warm water for 5 minutes
dry area thoroughly
using the applicator(cotton swab),apply alayer of ointment to sufhcientlycovereachwart
allow it to fully absorb and cover it withobandage as needed.
repeat this procedure once or twice dailyasneeded (until the wart is removed) for upto12 weeks

INACTIVE INGREDIENT

Brucea javanica
Rhizoma coptidis
Cantharides
calamus
pepper
osthole
Phellodendron
Sophora flavescens
camphor
borneol
glycerin
ethanol